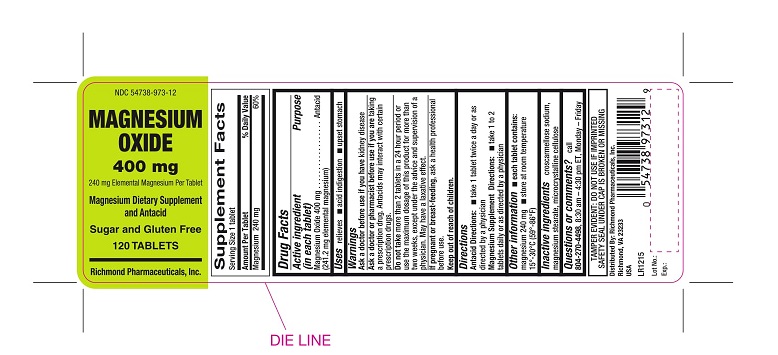 DRUG LABEL: Magnesium Oxide
NDC: 54738-973 | Form: TABLET
Manufacturer: Richmond Pharmaceuticals, Inc.
Category: otc | Type: HUMAN OTC DRUG LABEL
Date: 20241226

ACTIVE INGREDIENTS: MAGNESIUM OXIDE 400 mg/1 1
INACTIVE INGREDIENTS: CROSCARMELLOSE SODIUM; CELLULOSE, MICROCRYSTALLINE; MAGNESIUM STEARATE

Magnesium Oxide Tablets

ACTIVE INGREDIENT (In each tablet)

Magnesium Oxide 400mg (241.2mg elemental magnesium)

Purpose

Antacid

USES

Relieves: ■ acid indigestion ■ upset stomach

WARNINGS

Ask a doctor if you have:

kidney disease

Ask a doctor or pharmacist before use if you are:

taking a prescription drug. Antacids may interact with certain prescription drugs.

Do not take

more than 2 tablets in a 24 hour period or use the maximum dosage of this product for more than two weeks, except under the advise and supervision of a physician. May have a laxative effect.

If pregnant or breast-feeding,

ask a health professional before use.

DIRECTIONS

Antacid Directions:■ take 1 tablet twice a day or as directed by a physician

Magnesium Supplement Directions: ■take 1 to 2 tablets daily or as directed by a physician

OTHER INFORMATION

■ store at room temperature 59°-86° F (15°-30°C) ■ do not use if imprinted safety seal under cap is broken or missing

■ Magnesium content per tablet: 253 mg

INACTIVE INGREDIENTS

croscarmellose sodium, microcrystalline cellulose, magnesium stearate

Questions or Comments

TAMPER EVIDENT: DO NOT USE IF IMPRINTED SAFETY SEAL UNDER CAP IS BROKEN OR MISSING
call 804-270-4498, 8.30 am-4.30 pm ET, Monday - Friday

PRINCIPAL DISPLAY PANEL

NDC 54738-973-12- 120 tablets